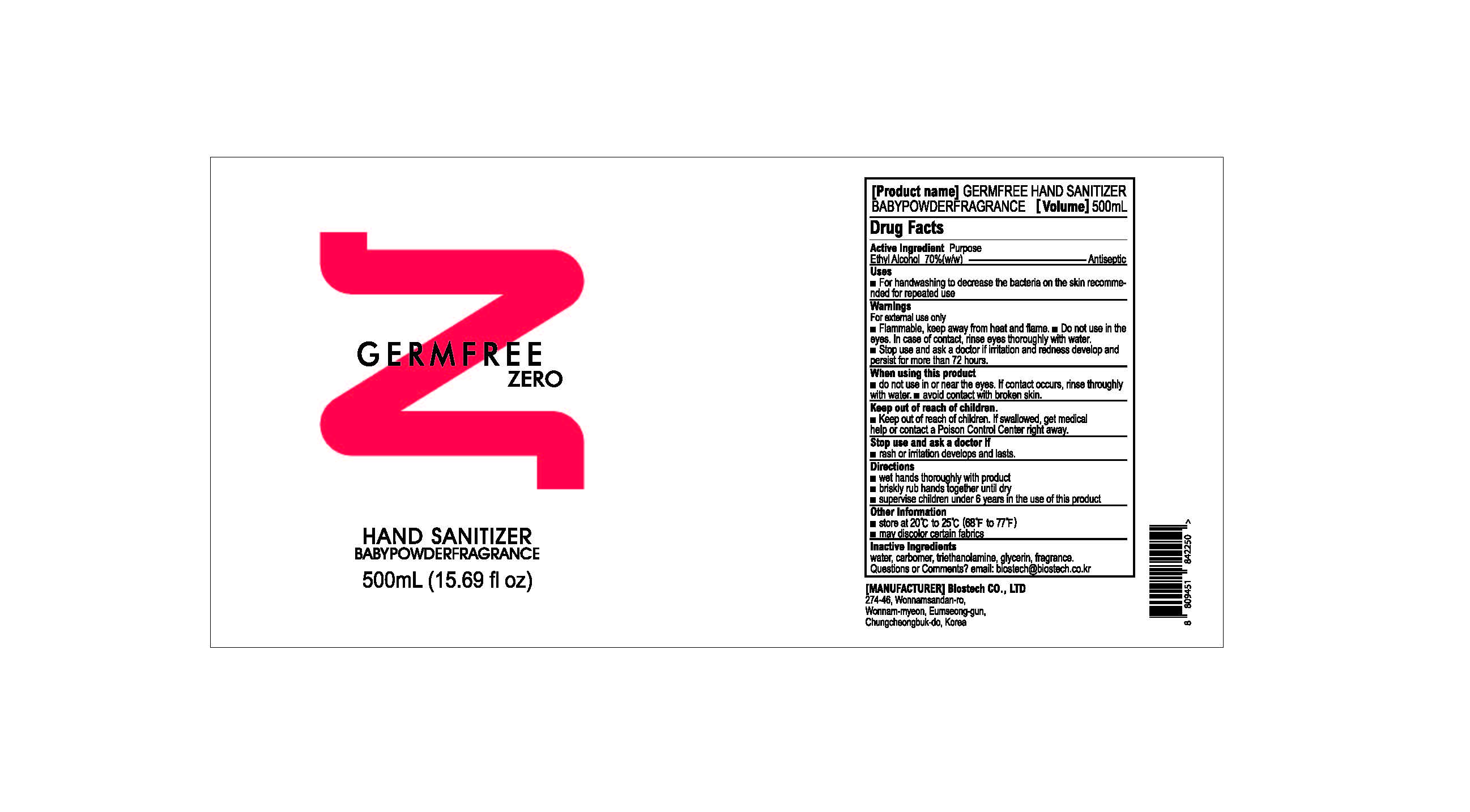 DRUG LABEL: GERMFREE HAND SANITIZER Gel babypowder fragrance
NDC: 70812-003 | Form: GEL
Manufacturer: BIOSTECH CO., LTD.
Category: otc | Type: HUMAN OTC DRUG LABEL
Date: 20200514

ACTIVE INGREDIENTS: ALCOHOL 350 mL/500 mL
INACTIVE INGREDIENTS: WATER; TROLAMINE; CARBOMER HOMOPOLYMER, UNSPECIFIED TYPE; GLYCERIN

ACTIVE INGREDIENT

Alcohol (Ethanol)

INACTIVE INGREDIENT

Glycerin, Triethanolamine, Carbomer, Fragrance, Water

PURPOSE

Antiseptic

keep out of reach of the children

do not use in or near the eyes. If contact occurs, rinse thoroughly with water.
avoid contact with broken skin.

WARNINGS

For external use only.
Flammable, keep away from heat and flame.
Do not use in the eyes. In case of contact, rinse eyes thoroughly with water.
Stop use and ask a doctor if irritation and redness develop and persist for more than 72 hours.

DOSAGE AND ADMINISTRATION

wet hands thoroughly with product briskly rub hands together until dry supervise children under 6 years in the use of this product